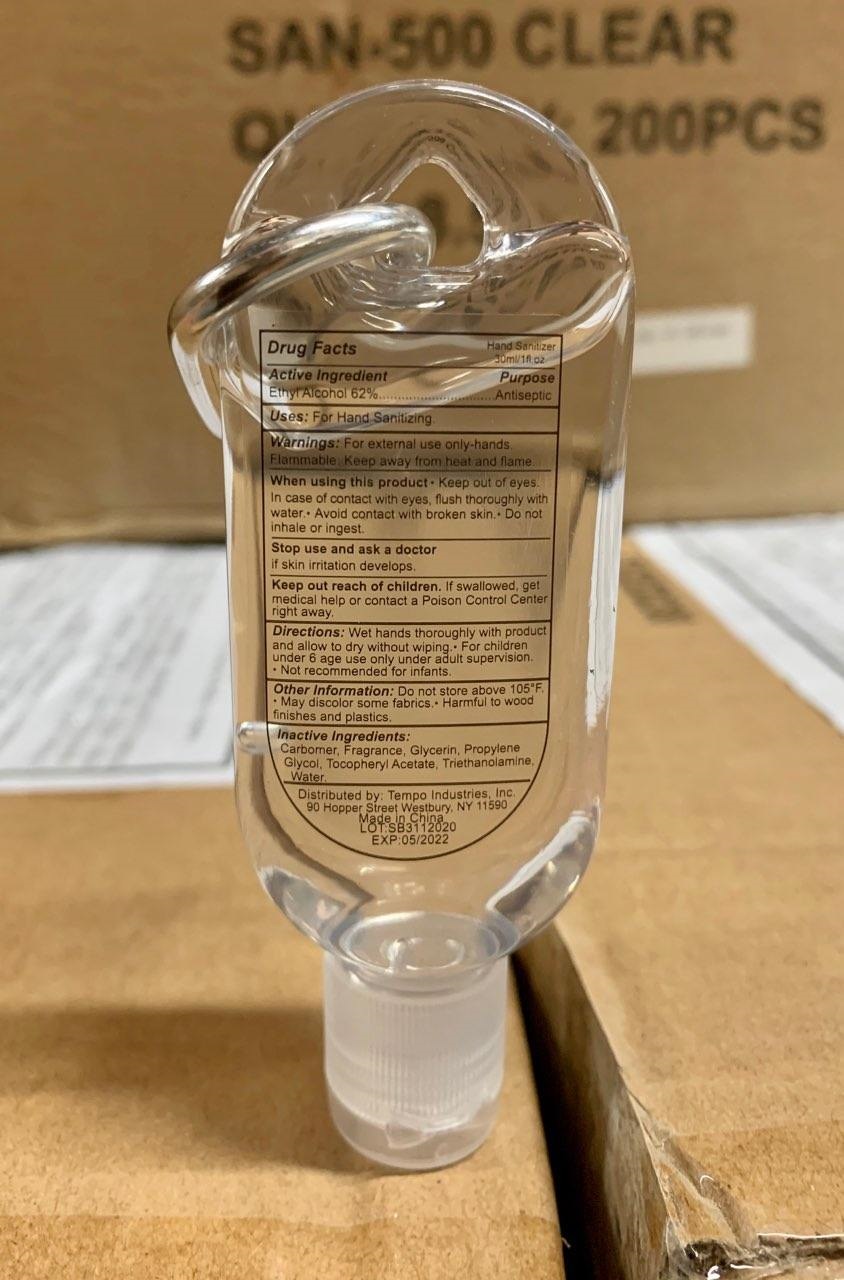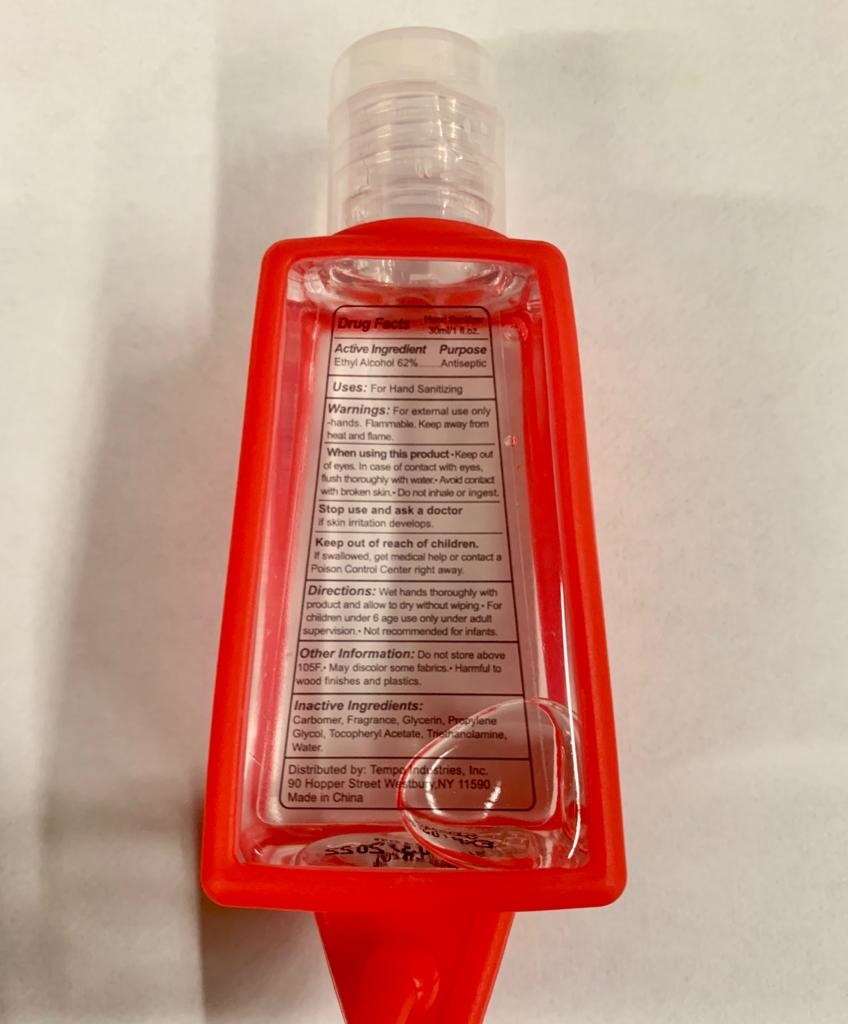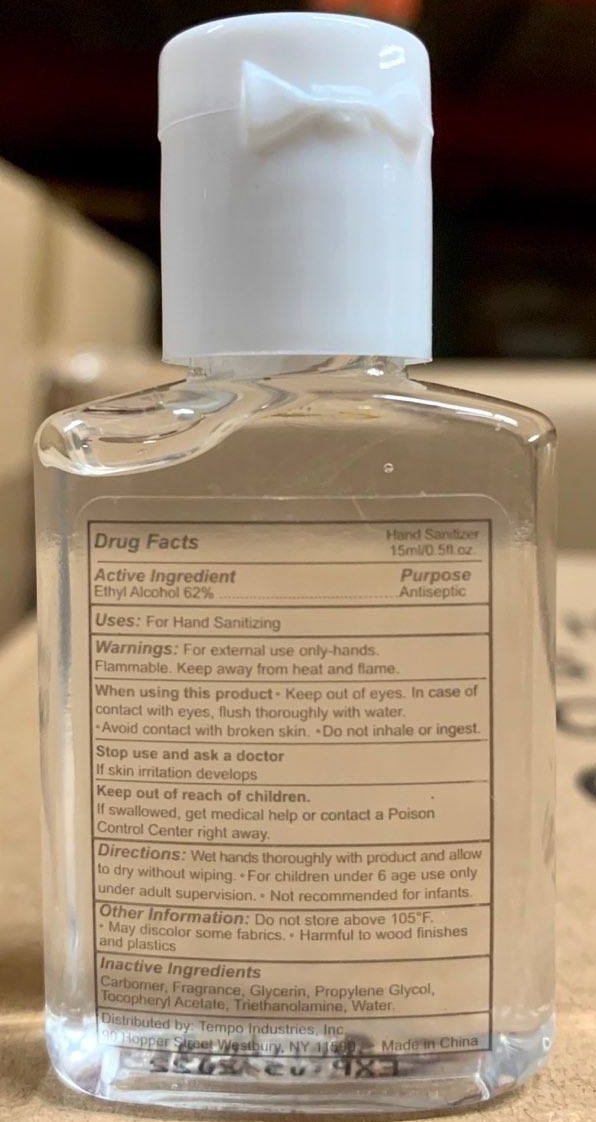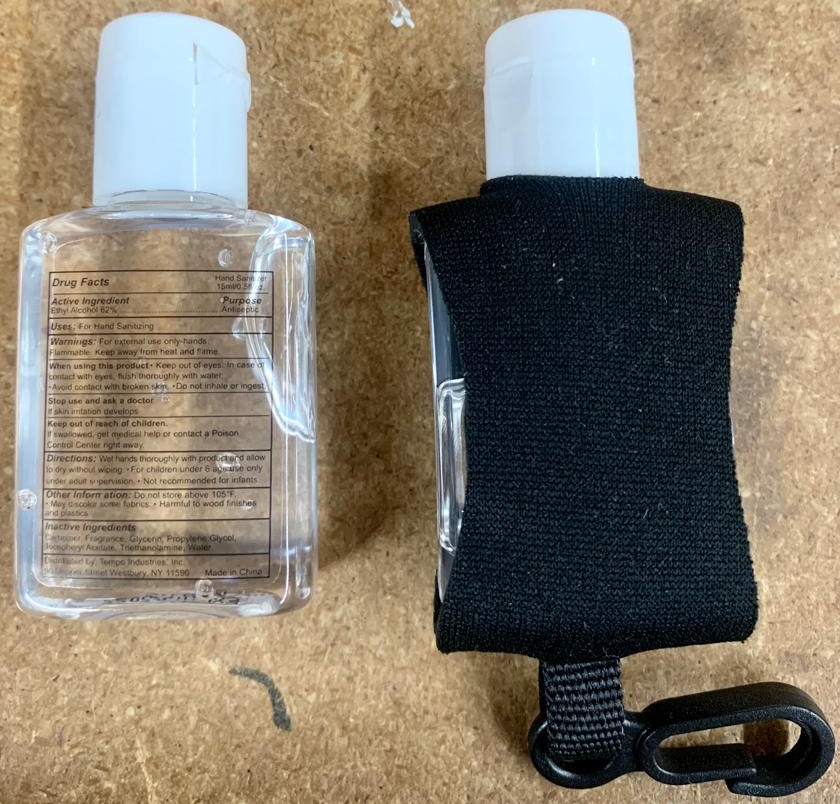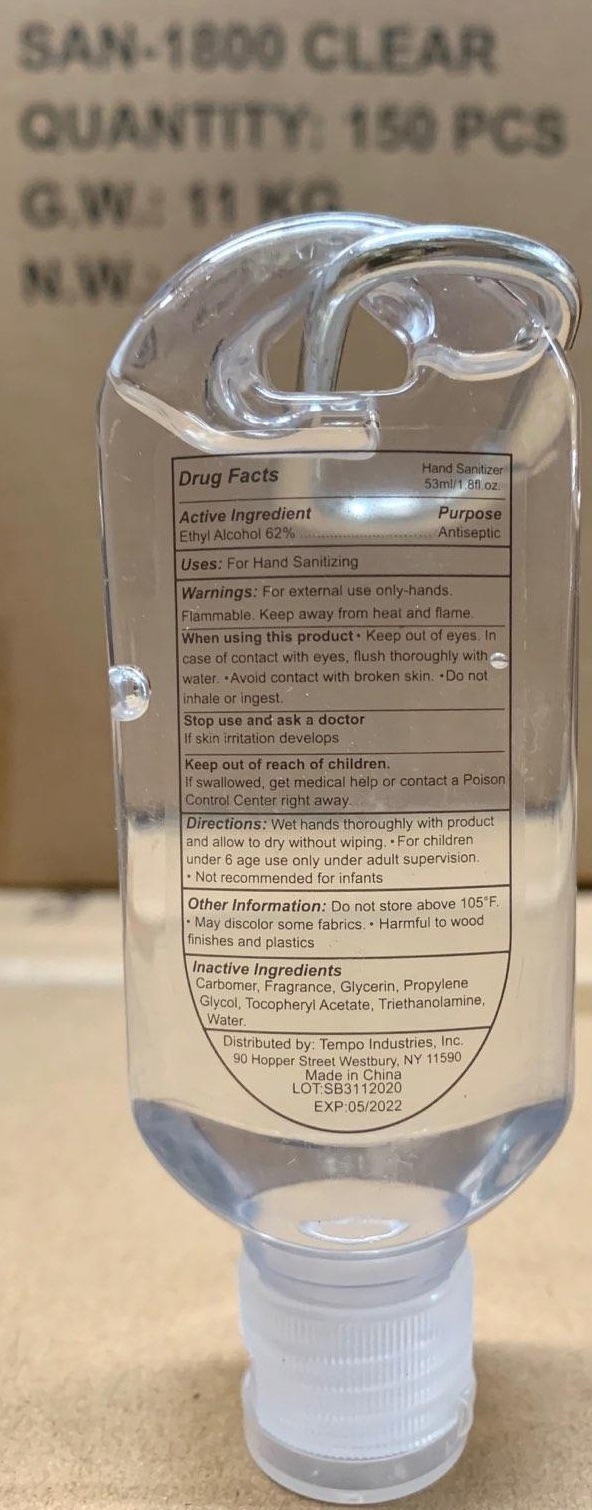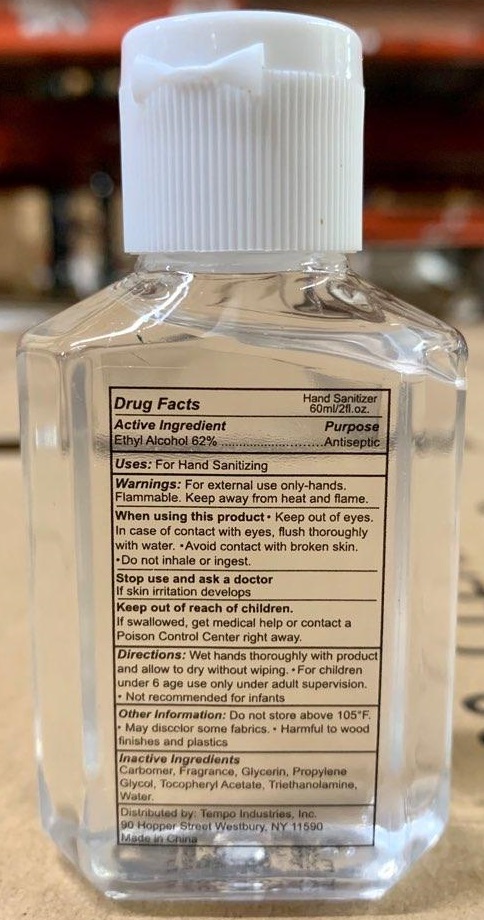 DRUG LABEL: Hand Sanitizer
NDC: 80524-000 | Form: GEL
Manufacturer: Tempo Industries, Inc.
Category: otc | Type: HUMAN OTC DRUG LABEL
Date: 20250108

ACTIVE INGREDIENTS: ALCOHOL 0.62 mL/1 mL
INACTIVE INGREDIENTS: CARBOMER HOMOPOLYMER, UNSPECIFIED TYPE; GLYCERIN; PROPYLENE GLYCOL; .ALPHA.-TOCOPHEROL ACETATE; TROLAMINE; WATER

Hand Sanitizer

Active Ingredient

Ethyl Alcohol 62%

Purpose

Antiseptic

Uses:

For Hand Sanitizing

Warnings:

For external use only-hands.

Flammable. Keep away from heat and flame.

When using this product

- Keep out of eyes. In case of contact with eyes, flush thoroughly with water
- Avoid contact with broken skin.
- Do not inhale or ingest.

Stop use and ask a doctor

If skin irritation develops

Keep out of reach of children

If swallowed, get medical help or contact a Poison Control Center right away.

Directions:

- Wet hands thoroughly with product and allow to dry without wiping.
- For children under 6 age use only under adult supervision.
- Not recommended for infants

Other Information:

- Do not store above 105°F.
- May discolor some fabrics.
- Harmful to wood finishes and plastics

Inactive Ingredients

Carbomer, Fragrance, Glycerin, Propylene Glycol, Tocopheryl Acetate, Triethanolamine, Water.